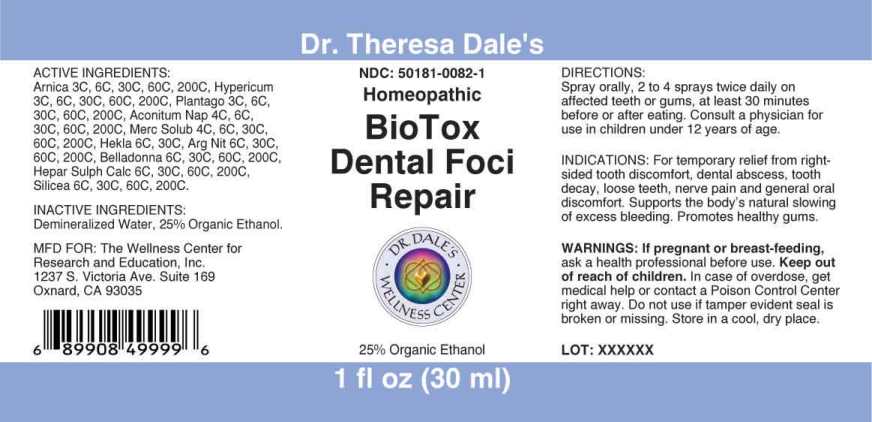 DRUG LABEL: BioTox Dental Foci Repair
NDC: 50181-0082 | Form: SPRAY
Manufacturer: The Wellness Center For Research and Education
Category: homeopathic | Type: HUMAN OTC DRUG LABEL
Date: 20250606

ACTIVE INGREDIENTS: ARNICA MONTANA WHOLE 3 [hp_C]/1 mL; HYPERICUM PERFORATUM WHOLE 3 [hp_C]/1 mL; PLANTAGO MAJOR WHOLE 3 [hp_C]/1 mL; ACONITUM NAPELLUS WHOLE 4 [hp_C]/1 mL; MERCURIUS SOLUBILIS 4 [hp_C]/1 mL; HEKLA LAVA 6 [hp_C]/1 mL; SILVER NITRATE 6 [hp_C]/1 mL; ATROPA BELLADONNA 6 [hp_C]/1 mL; CALCIUM SULFIDE 6 [hp_C]/1 mL; SILICON DIOXIDE 6 [hp_C]/1 mL
INACTIVE INGREDIENTS: WATER; ALCOHOL

DRUG FACTS:

ACTIVE INGREDIENTS:

Arnica Montana 3C, 6C, 30C, 60C, 200C, Hypericum Perforatum 3C, 6C, 30C, 60C, 200C, Plantago Major 3C, 6C, 30C, 60C, 200C, Aconitum Napellus 4C, 6C, 30C, 60C,200C, Mercurius Solubilis 4C, 6C, 30C, 60C,200C, Hekla Lava 6C, 30C, Argentum Nitricum 6C, 30C, 60C, 200C, Belladonna 6C, 30C, 60C, 200C, Hepar Sulphuris Calcareum 6C, 30C, 60C, 200C, Silicea 6C, 30C, 60C, 200C.

INDICATIONS:

For Temporary relief from right-sided tooth discomfort, dental abscess, tooth decay, loose teeth, nerve pain and general oral discomfort, Supports the body's natural slowing of excess bleeding. Promotes healthy gums.

WARNINGS:

If pregnant or breast-feeding, ask a health professional before use.

Keep out of reach of children. In case of overdose, get medical help or contact a Poison Control Center right away.

Do not use if tamper evident seal is broken or missing.

Store in a cool, dry place.

Keep out of reach of children. In case of overdose, get medical help or contact a Poison Control Center right away.

DIRECTIONS:

Spray orally, 2 to 4 sprays twice daily on affected teeth or gums, at least 30 minutes before or after eating. Consult a physician for use in children under 12 years of age.

INDICATIONS:

For Temporary relief from right-sided tooth discomfort, dental abscess, tooth decay, loose teeth, nerve pain and general oral discomfort, Supports the body's natural slowing of excess bleeding. Promotes healthy gums.

INACTIVE INGREDIENTS:

Demineralized Water, 25% Organic Ethanol.

QUESTONS:

MFD FOR: The Wellness Center for

Research and Education, Inc.

1237 S. Victoria Ave. Suite 169

Oxnard, CA 93035

PACKAGE LABEL DISPLAY:

Dr. Theresa Dale's

NDC 50181-0082-1

Homeopathic

BioTox

Dental Foci

Repair

1 fl oz (30 ml)